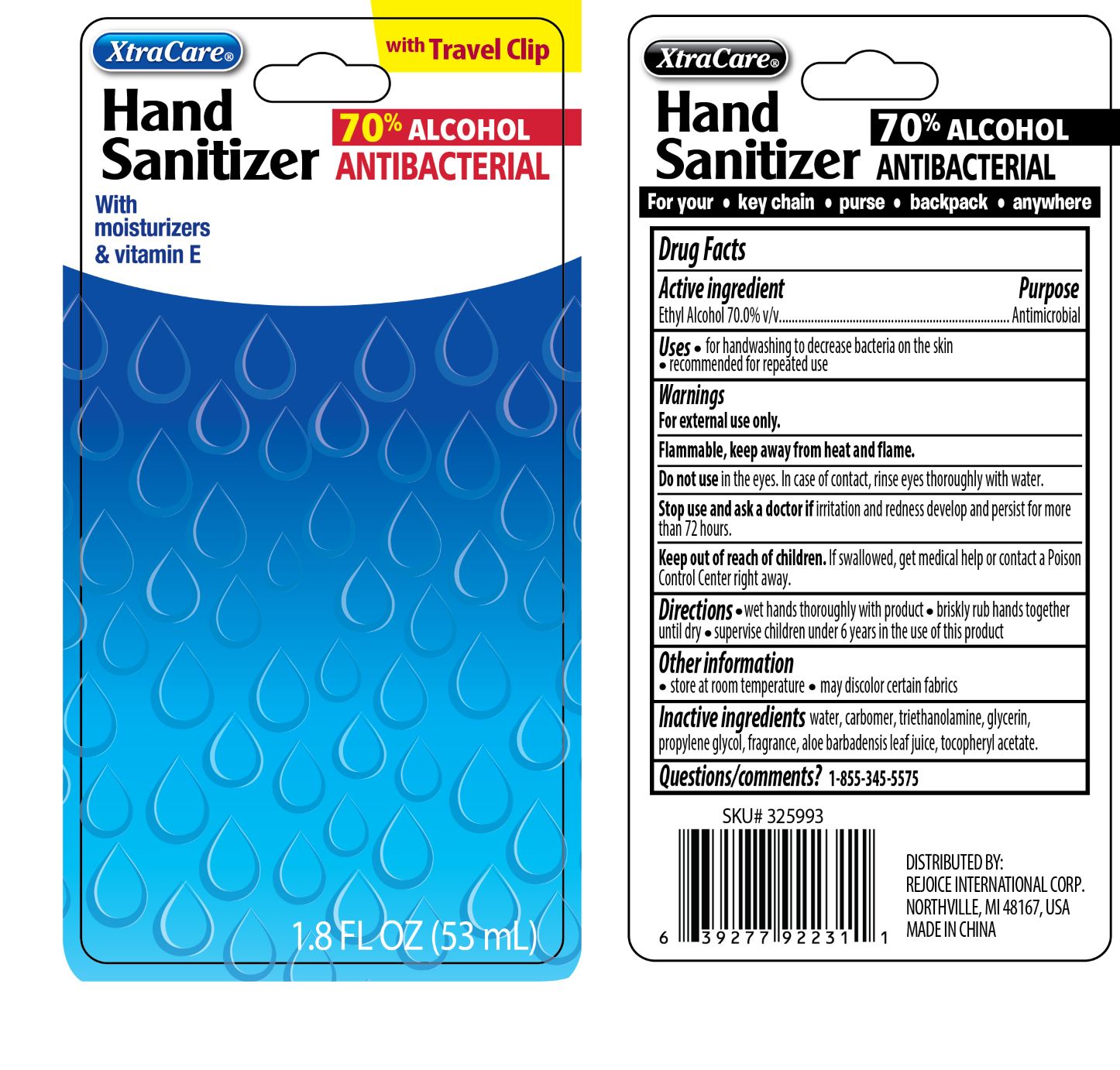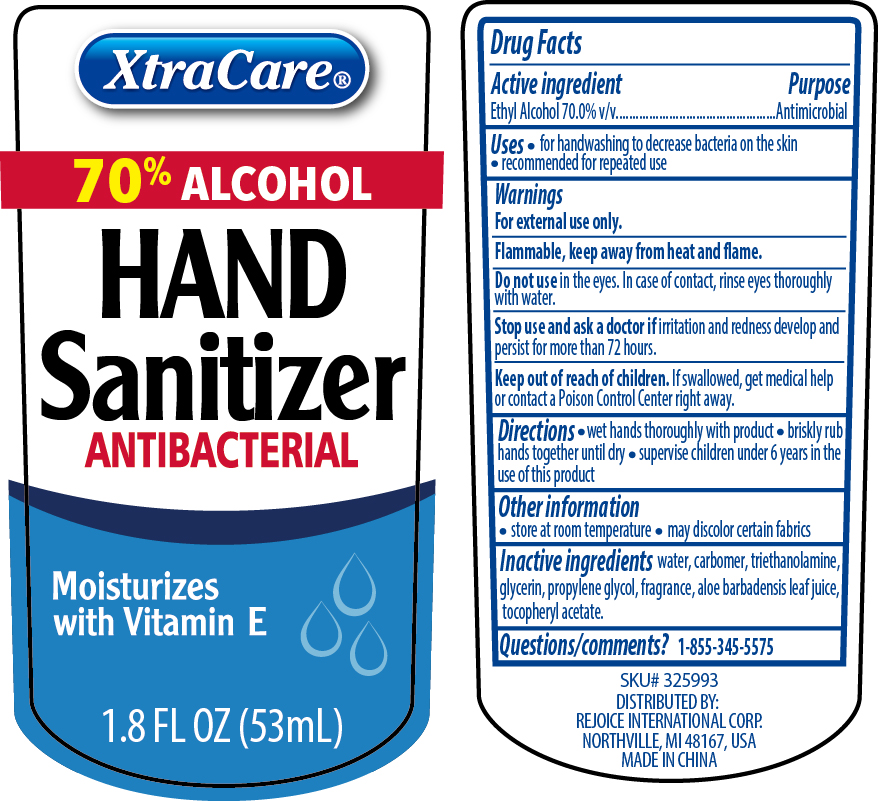 DRUG LABEL: Hand Sanitizer with Clip
NDC: 57337-125 | Form: LIQUID
Manufacturer: Ningbo Rejoice International
Category: otc | Type: HUMAN OTC DRUG LABEL
Date: 20250213

ACTIVE INGREDIENTS: ALCOHOL 70 mL/100 mL
INACTIVE INGREDIENTS: WATER; TROLAMINE; PROPYLENE GLYCOL; GLYCERIN; ALOE; CARBOMER HOMOPOLYMER, UNSPECIFIED TYPE; ALPHA-TOCOPHEROL ACETATE

Hand Sanitizer with Clip

Active Ingredient(s)

Ethyl Alcohol 70% v/v.

Purpose

Antimicrobial

Use

- for handwashing to decrease bacteria on the skin
- recommended for repeated use

Warnings

For external use only. Flammable, keep away from heat and flame

Do not use

- in the eyes. In case of contact, rinse eyes thoroughly with water.

Stop use and ask a doctor if irritation or rednees develp and persist for more than 72 hours.

Keep out of reach of children. If swallowed, get medical help or contact a Poison Control Center right away.

Directions

- Wet hand thoroughly with product
- briskly rub hands together until dry.
- Supervise children under 6 years of age when using this product to avoid swallowing.

Other information

- Store at room temperature
- may discolor certain fabrics

Inactive ingredients

water, carbomer, triethanolamine, glycerin, propylene glycol, fragrance, aloe barbadensis leaf juice, tocopheryl acetate.

QUESTIONS

1-855-345-5575